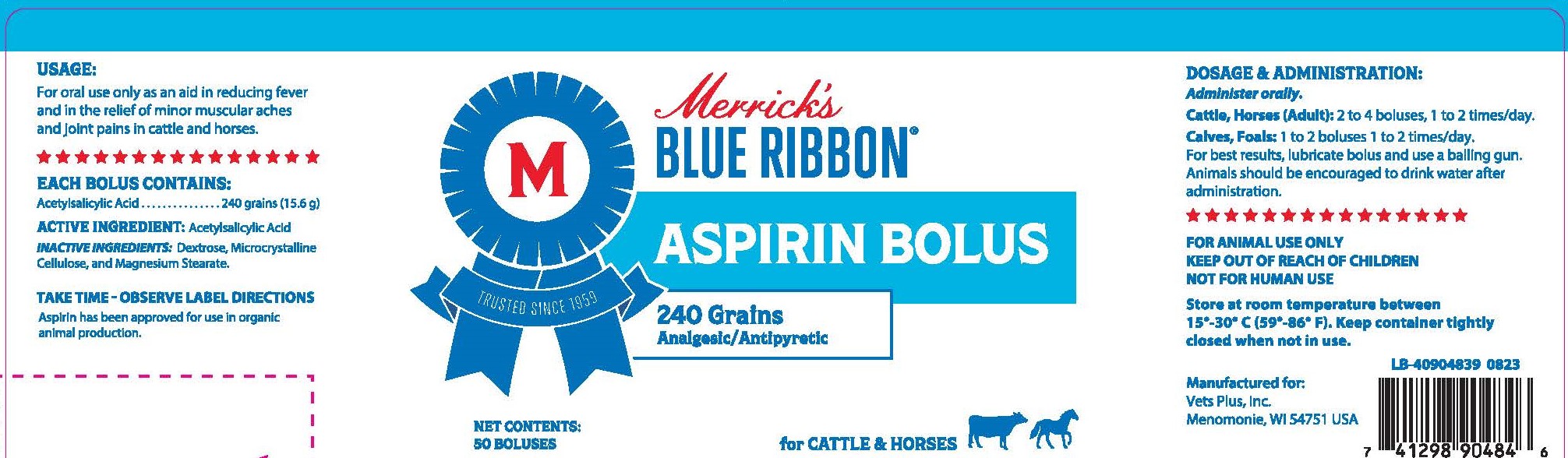 DRUG LABEL: MBR Aspirin Bolus 240 Grains
NDC: 86118-240 | Form: TABLET
Manufacturer: Merrick's Animal Health, LLC.
Category: animal | Type: OTC ANIMAL DRUG LABEL
Date: 20250113

ACTIVE INGREDIENTS: ASPIRIN 15.6 g/1 1

Usage:

For oral use only as an aid in reducing fever and in the relief of minor muscular aches and joint pains in cattle and horses.

Dosage and Administration:

Administer orally

Cattle, Horses (Adult): 2 to 4 boluses 1 to 2 times/day.

Calves, Foals: 1 to 2 boluses 1 to 2 times/day.

For best results, lubricate bolus and use a balling gun. Animals should be encouraged to drink water after administration.

Each Bolus Contains:

Acetylsalicylic Acid............240 grains (15.6g)

Active Ingredient:

Acetylsalicylic Acid

Inactive Ingredients:

Dextrose, Microcrystalline Cellulose, and Magnesium Stearate.

STORAGE AND HANDLING

Store at room temperature between 15°-30°C (59°-86°F). Keep container tightly closed when not in use.

KEEP OUT OF REACH OF CHILDREN

FOR ANIMAL USE ONLY

KEEP OUT OF REACH OF CHILDREN

NOT FOR HUMAN USE

PACKAGE LABEL

Add image transcription here...

Add image transcription here...